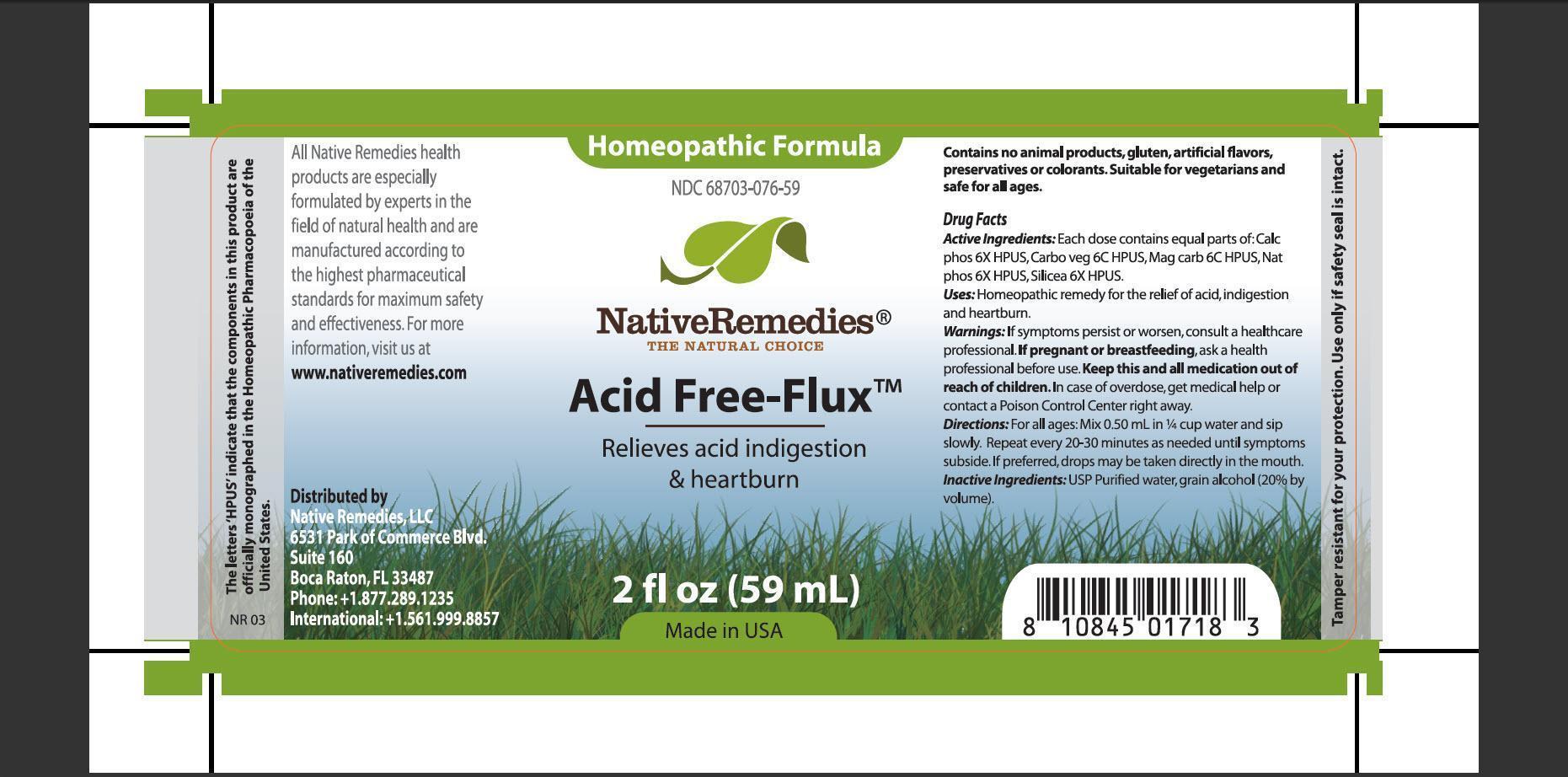 DRUG LABEL: Acid Free-Flux
NDC: 68703-076 | Form: TINCTURE
Manufacturer: Native Remedies, LLC
Category: homeopathic | Type: HUMAN OTC DRUG LABEL
Date: 20130424

ACTIVE INGREDIENTS: TRIBASIC CALCIUM PHOSPHATE 6 [hp_X]/1 mL; ACTIVATED CHARCOAL 6 [hp_C]/1 mL; MAGNESIUM CARBONATE 6 [hp_C]/1 mL; SODIUM PHOSPHATE, DIBASIC, HEPTAHYDRATE 6 [hp_X]/1 mL; SILICON DIOXIDE 6 [hp_X]/1 mL
INACTIVE INGREDIENTS: WATER; ALCOHOL

Acid Free-Flux

PURPOSE

Relieves acid indigestion and heartburn

ACTIVE INGREDIENT

Active Ingredients: Each dose contains equal parts of: Calc phos 6X HPUS, Carbo veg 6C HPUS, Mag carb 6C HPUS, Nat phos 6X HPUS, Silicea 6X HPUS

INDICATIONS AND USAGE

Uses: Homeopathic remedy for the relief of acid, indigestion and heartburn

WARNINGS

Warnings: If symptoms persist or worsen, consult a health professional

PREGNANCY OR BREAST FEEDING

If pregnant or breastfeeding, ask a heath professional before use

KEEP OUT OF REACH OF CHILDREN

Keep this and all medication out of reach of children

OVERDOSAGE

In case of overdose, get medical help or contact a Poison Control Center right away

DOSAGE AND ADMINISTRATION

Directions: For all ages: Mix 0.50 mL in 1/4 cup water and sip slowly. Repeat every 20-30 minutes as needed until symptoms subside. If preferred, drops may be taken directly in the mouth

INACTIVE INGREDIENT

Inactive Ingredients: USP Purified water, grain alcohol (20% by volume)

PATIENT COUNSELING INFORMATION

The letters 'HPUS' indicate that the component in this product are officially monographed in the Homeopathic Pharmacopoeia of the United States

All Native Remedies health products are especially formulated by experts in the field of natural health and are manufactured according to the highest pharmaceutical standards for maximum safety and effectiveness. For more information, visit us at www.nativeremedies.com

Distributed by
Native Remedies, LLC
6531 Park of Commerce Blvd.
Suite 160
Boca Raton, FL 33487
Phone:+1.877.289.1235
International:+1.561.999.8857

Contains no animal products, gluten artificial flavors, preservatives or colorants. Suitable for vegetarians and safe for all ages

STORAGE AND HANDLING

Tamper resistant for your protection. Use only if safety seal is intact